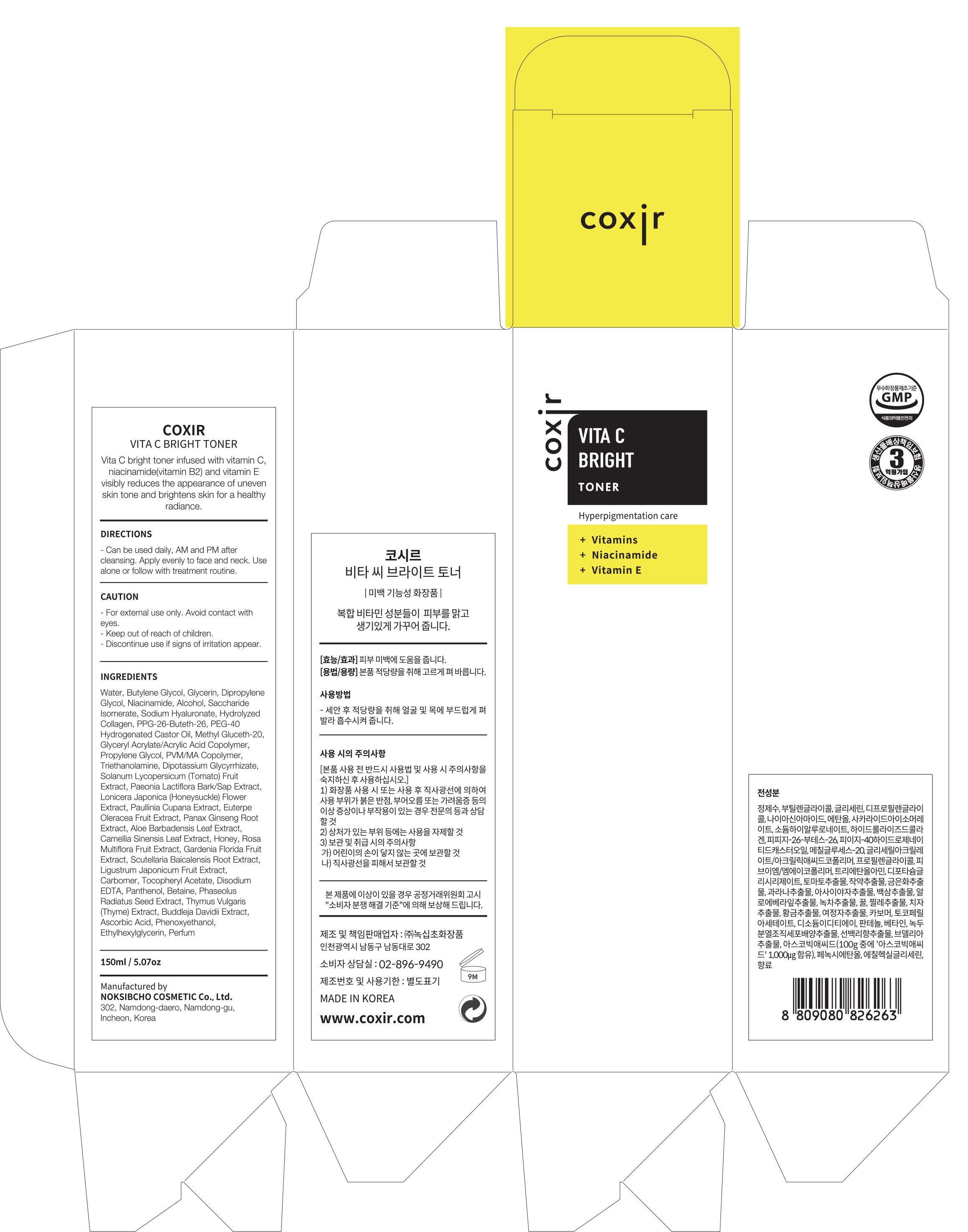 DRUG LABEL: Vita C Bright Toner
NDC: 73590-0018 | Form: LIQUID
Manufacturer: NOKSIBCHO cosmetic Co., Ltd.
Category: otc | Type: HUMAN OTC DRUG LABEL
Date: 20200314

ACTIVE INGREDIENTS: NIACINAMIDE 2 g/100 mL
INACTIVE INGREDIENTS: WATER; BUTYLENE GLYCOL

Drug Facts

ACTIVE INGREDIENT

niacinamide, vitamins, vitamin E

INACTIVE INGREDIENT

Water
Butylene glycol
Glycerin
Dipropylene Glycol
Niacinamide
Alcohol
Saccharide Isomerate
Sodium Hyaluronate
Hydrolyzed Collagen
PPG-26-Buteth-26
PEG-40 Hydrogenated Castor Oil
Methyl Gluceth-20
Glycerin
Glyceryl Acrylate/Acrylic Acid Copolymer
Propylene Glycol
PVM/MA Copolymer
Triethanolamine
Dipotassium Glycyrrhizate
Solanum Lycopersicum (Tomato) Fruit Extract
Paeonia Lactiflora Bark/Sap Extract
Lonicera Japonica (Honeysuckle) Flower Extract
Paullinia Cupana Extract
Euterpe Oleracea Fruit Extract
Panax Ginseng Root Extract
Aloe Barbadensis Leaf Extract
Camellia Sinensis Leaf Extract
Honey
Rosa Multiflora Fruit Extract
Gardenia Florida Fruit Extract
Scutellaria Baicalensis Root Extract
Ligustrum Japonicum Fruit Extract
Carbomer
Tocopheryl Acetate
Disodium EDTA
Carbomer
Panthenol
Betaine
Phaseolus Radiatus Meristem Cell Culture Extract
Camellia Sinensis Callus Culture Extract
Thymus Vulgaris (Thyme) Extract
Buddleja Davidii Extract
Ascorbic Acid
Phenoxyethanol
Ethylhexylglycerin
Parfum

PURPOSE

hyperpigmentation care

keep out of reach of the children

INDICATIONS AND USAGE

apply proper amount and gently massage

WARNINGS

For external use only
When using this product

■ if the following symptoms occurs after use, stop use and consult with a skin specialist

red specks, swelling, itching

■ don’t use on the part where there is injury, eczema, or dermatitis

Keep out of reach of children

■ if swallowed, get medical help or contact a person control center immediately

DOSAGE AND ADMINISTRATION

for external use only